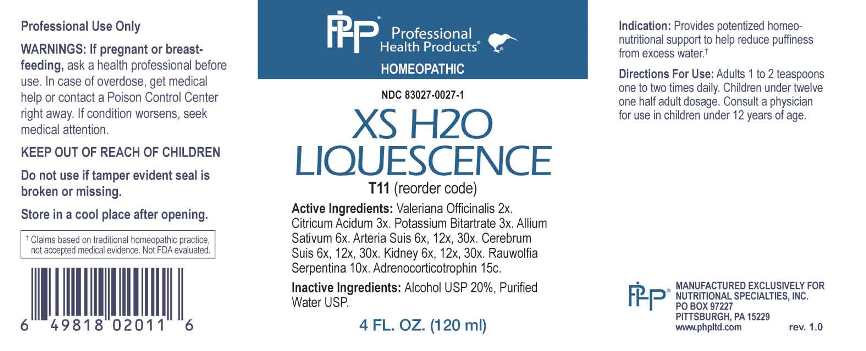 DRUG LABEL: XS H2O Liquescence
NDC: 83027-0027 | Form: LIQUID
Manufacturer: Nutritional Specialties, Inc.
Category: homeopathic | Type: HUMAN OTC DRUG LABEL
Date: 20241031

ACTIVE INGREDIENTS: VALERIAN 2 [hp_X]/1 mL; ANHYDROUS CITRIC ACID 3 [hp_X]/1 mL; POTASSIUM BITARTRATE 3 [hp_X]/1 mL; GARLIC 6 [hp_X]/1 mL; SUS SCROFA ARTERY 6 [hp_X]/1 mL; SUS SCROFA CEREBRUM 6 [hp_X]/1 mL; PORK KIDNEY 6 [hp_X]/1 mL; RAUWOLFIA SERPENTINA 10 [hp_X]/1 mL; CORTICOTROPIN 15 [hp_C]/1 mL
INACTIVE INGREDIENTS: WATER; ALCOHOL

DRUG FACTS:

ACTIVE INGREDIENTS:

Valeriana Officinalis 2X, Citricum Acidum 3X, Potassium Bitartrate 3X, Allium Sativum 6X, Arteria Suis 6X, 12X, 30X, Cerebrum Suis 6X, 12X, 30X, Kidney 6X, 12X, 30X, Rauwolfia Serpentina 10X, Adrenocorticotrophin 15C.

PURPOSE:

Provides potentized homeo-nutritional support to help reduce puffiness from excess water.†

†Claims based on traditional homeopathic practice, not accepted medical evidence. Not FDA evaluated.

WARNINGS:

Professional Use Only

If pregnant or breast-feeding, ask a health professional before use.

In case of overdose, get medical help or contact a Poison Control Center right away.

If condition worsens, seek medical attention.

KEEP OUT OF REACH OF CHILDREN

Do not use if tamper evident seal is broken or missing.

Store in a cool place after opening

KEEP OUT OF REACH OF CHILDREN:

In case of overdose, get medical help or contact a Poison Control Center right away.

DIRECTIONS:

Adults 1 to 2 teaspoons one to two times daily. Children under twelve one half adult dosage. Consult a physician for use in children under 12 years of age.

INDICATIONS:

Provides potentized homeo-nutritional support to help reduce puffiness from excess water.†

†Claims based on traditional homeopathic practice, not accepted medical evidence. Not FDA evaluated.

INACTIVE INGREDIENTS:

Alcohol USP 20%, Purified Water USP.

QUESTIONS:

MANUFACTURED EXCLUSIVELY FOR

NUTRITIONAL SPECIALTIES, INC.

PO BOX 97227

PITTSBURG, PA 15229

www.phpltd.com

PACKAGE LABEL DISPLAY:

Professional

Health Products

HOMEOPATHIC

NDC 83027-0027-1

XS H2O

LIQUESCENCE

4 FL. OZ. (120 ml)